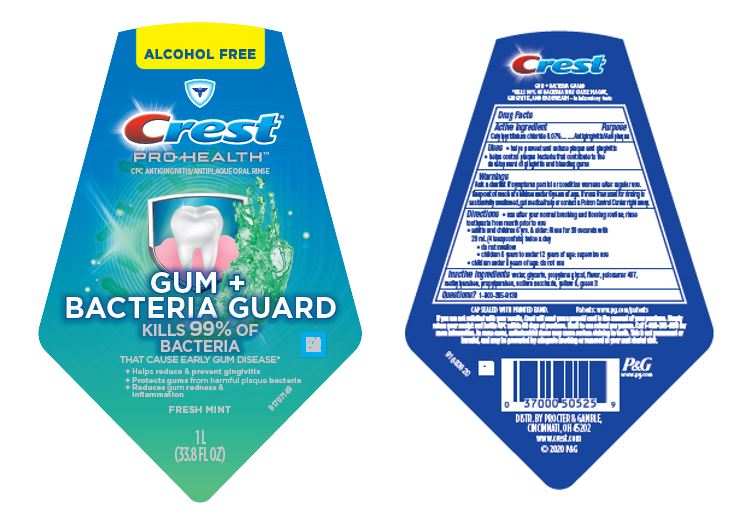 DRUG LABEL: Crest Pro Health
NDC: 69423-931 | Form: RINSE
Manufacturer: The Procter & Gamble Manufacturing Company
Category: otc | Type: HUMAN OTC DRUG LABEL
Date: 20250806

ACTIVE INGREDIENTS: CETYLPYRIDINIUM CHLORIDE 0.014 g/1 mL
INACTIVE INGREDIENTS: PROPYLPARABEN; WATER; METHYLPARABEN; GLYCERIN; PROPYLENE GLYCOL; POLOXAMER 407; SACCHARIN SODIUM; FD&C YELLOW NO. 6; FD&C GREEN NO. 3

Crest Pro Health Gum plus Bacteria Guard

Drug Facts

Active ingredient

Cetylpyridinium chloride 0.07%

Purpose

Antigingivitis/Antiplaque

Uses

- helps prevent and reduce plaque and gingivitis
- helps control plaque bacteria that contribute to the development of gingivitis and bleeding gums

Warnings

ASK DOCTOR

Ask a dentist if symptoms persist or condition worsens after regular use.

Keep out of reach of children under 6 years of age. If more than used for rinsing is accidentally swallowed, get medical help or contact a Poison Control Center right away.

Directions

- use after your normal brushing and flossing routine; rinse toothpaste from mouth prior to use
- adults and children 6 yrs. & older: Rinse for 30 seconds with 20 mL (4 teaspoonfuls) twice a day
  - do not swallow
  - children 6 years to under 12 years of age: supervise use
- children under 6 years of age: do not use

Inactive ingredients

water, glycerin, propylene glycol, flavor, poloxamer 407, methylparaben, propylparaben, sodium saccharin, yellow 6, green 3

Questions?

1–800–285-9139

PRINCIPAL DISPLAY PANEL - 1000 mL Bottle Label

ALCOHOL FREE

Crest®
PRO HEALTH
CPC ANTIGINGIVITIS/ANTIPLAQUE ORAL RINSE

GUM + BACTERIA GUARD

KILLS 99% OF BACTERIA

THAT CAUSE EARLY GUM DISEASE*

+ Helps reduce & prevent gingivitis
+ Protects gums from harmful plaque bacteria
+ Reduces gum redness & inflammation
FRESH MINT

1 L(33.8 FL OZ)